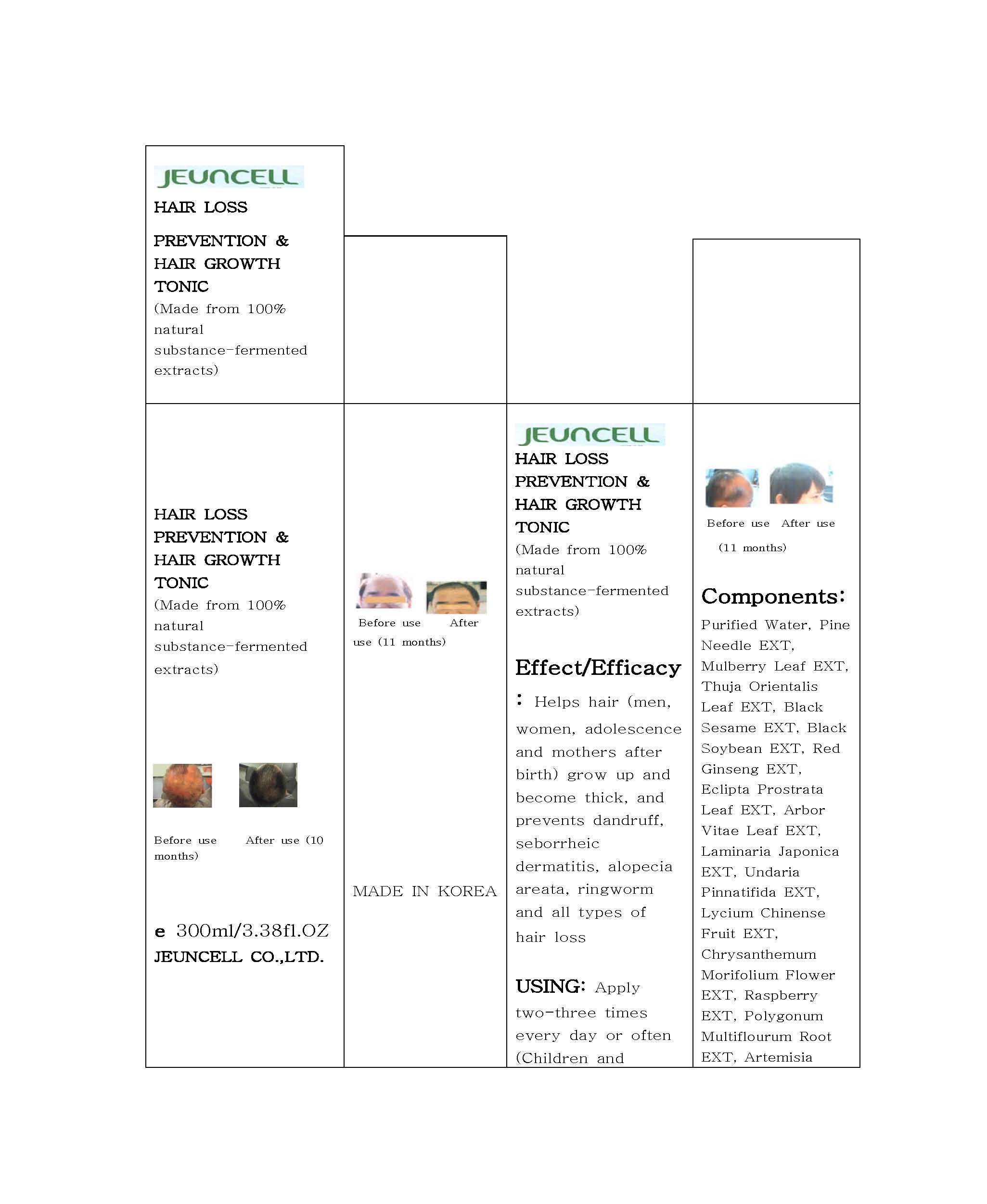 DRUG LABEL: JEUNCELL Hair Loss Prevention and Hair Growth Tonic
NDC: 54296-2001 | Form: LIQUID
Manufacturer: Jeun Cell Ltd
Category: otc | Type: HUMAN OTC DRUG LABEL
Date: 20121125

ACTIVE INGREDIENTS: PINE NEEDLE OIL (PINUS MUGO) 5 mg/100 mL
INACTIVE INGREDIENTS: MORUS ALBA LEAF; PLATYCLADUS ORIENTALIS LEAF; SESAME OIL; SOYBEAN; ASIAN GINSENG; ECLIPTA PROSTRATA LEAF; PLATYCLADUS ORIENTALIS POLLEN; LAMINARIA JAPONICA; UNDARIA PINNATIFIDA; LYCIUM CHINENSE FRUIT; CHRYSANTHEMUM X MORIFOLIUM FLOWER; RASPBERRY; FALLOPIA MULTIFLORA ROOT; ARTEMISIA VULGARIS TOP OIL; CNIDIUM OFFICINALE ROOT; GREEN TEA LEAF; PAPRIKA; ZANTHOXYLUM BUNGEANUM FRUIT

Drug Facts

ACTIVE INGREDIENT

pine needle extract

INACTIVE INGREDIENT

■ Pine Needle EXT ■ Mulberry Leaf EXT ■ Thuja Orientalis Leaf EXT ■ Black Sesame EXT ■ Black Soybean EXT ■ Red Ginseng EXT ■ Eclipta Prostrata Leaf EXT ■ Arbor Vitae Leaf EXT ■ Laminaria Japonica EXT ■ Undaria Pinnatifida
EXT ■ Lycium Chinense Fruit EXT ■ Chrysanthemum Morifolium Flower EXT ■Raspberry EXT ■ Polygonum Multiflourum Root EXT ■ Artemisia Vulgaris EXT ■ Cnidium Officinale Root EXT ■ Green Tea EXT ■ Capsicum Annuum Fruit EXT ■ Laminaria Japonica EXT ■ Zanthoxylum Bungeanum EXT

PURPOSE

hair loss prevention and hair growth

keep out of reach of the children

INDICATIONS AND USAGE

- applied area: skin
- apply two-three times every day or often to the atopies and itchy skin rashes
- apply sufficient quantity to the intended part

When using this product
- keep out of eyes, ears, and mouth. If contact occurs, rinse with plenty of cold water right away and contact a physician. If swallowing, drink plenty of water and contact a physician

DOSAGE AND ADMINISTRATION

for external use only